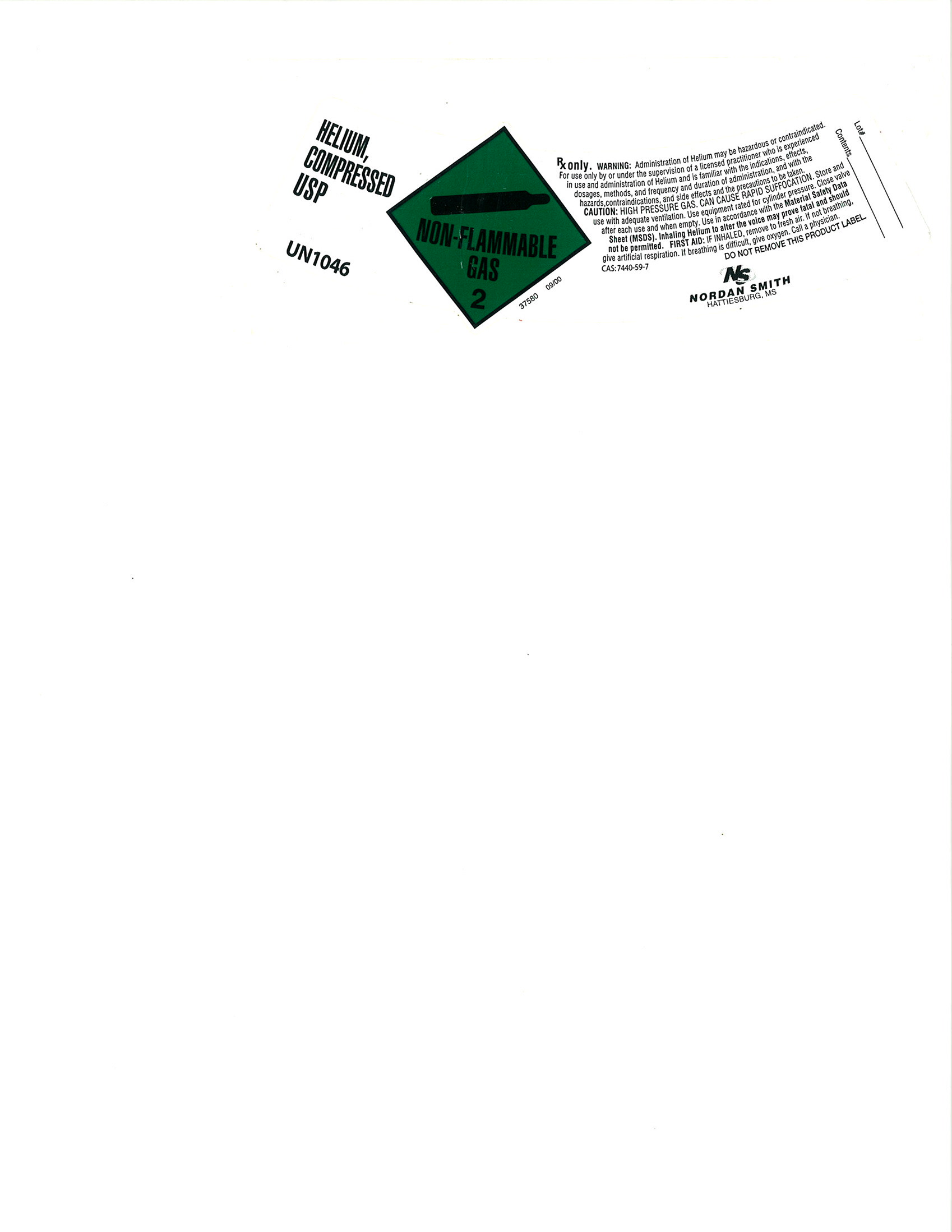 DRUG LABEL: Helium
NDC: 54416-005 | Form: GAS
Manufacturer: Nordan Smith Welding Supply
Category: prescription | Type: HUMAN PRESCRIPTION DRUG LABEL
Date: 20100813

ACTIVE INGREDIENTS: Helium 995 mL/1 L

Helium

PACKAGE LABEL

HELIUM, COMPRESSED USP
UN1046
NON-FLAMMABLE GAS 2
RX ONLY. WARNING: Administration of helium may be hazardous or contraindicated. For use only or under the supervision of a licensed practitioner who is experienced in use and administration of Helium and is familiar with the indications, effects, dosages, methods, and frequency and duration of administration, and with the hazards, contraindications, and side effects and the precautions to be taken. CAUTION: HIGH PRESSURE GAS, CAN CAUSE RAPID SUFFOCATION. Store and use with adequate ventilation. Use equipment rated for cylinder pressure. Close valve after each use and when empty. Use in accordance with the Material Safety Data Sheet (MSDS). Inhaling Helium to alter voice may prove fatal and should not be permitted. FIRST AID: IF INHALED, remove to fresh air. If not breathing give artificial respiration. If breathing is difficult, give oxygen. Call a physician.
CAS: 7440-59-7 DO NOT REMOVE THIS PRODUCT LABEL.
Lot#_________________ Contents____________________
N/S NORDAN SMITH HATTIESBURG, MS.
37580 09/00